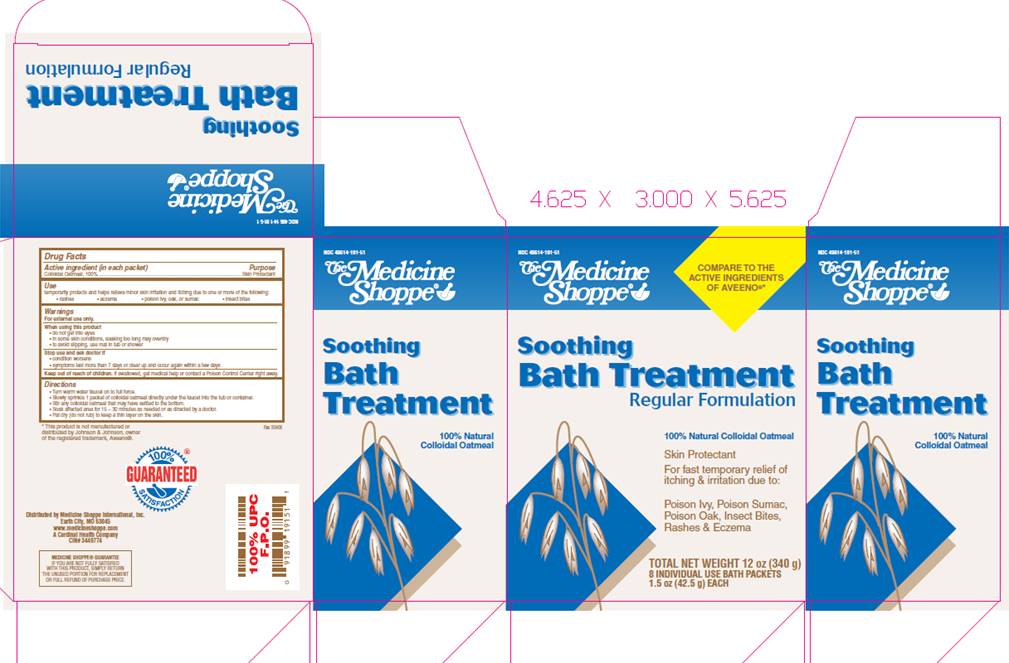 DRUG LABEL: Soothing Bath Treatment
NDC: 49614-191 | Form: POWDER
Manufacturer: Medicine Shoppe International Inc
Category: otc | Type: HUMAN OTC DRUG LABEL
Date: 20100315

ACTIVE INGREDIENTS: OATMEAL 1 g/1 g

DRUG FACTS

ACTIVE INGREDIENT (in each packet)

Colloidal Oatmeal, 100%

PURPOSE

Skin Protectant

USE

temporarily protects and helps relieve minor skin irritation and itching due to one or more of the following:

- rashes
- eczema
- poison ivy, oak, or sumac
- insect bites

WARNINGS

For external use only.

When using this product

- do not get into eyes
- in some skin conditions, soaking too long may overdry
- to avoid slipping, use mat in tub or shower

Stop use and ask doctor if

- condition worsens
- symptoms last more than 7 days or clear up and occur again within a few days

Keep out of reach of children.

If swallowed, get medical help or contact a Poison Control Center right away.

DIRECTIONS

- Turn warm water faucet on to full force.
- Slowly sprinkle 1 packet of colloidal oatmeal directly under the faucet into the tub or container.
- Stir any colloidal oatmeal that may have settled to the bottom.
- Soak affected area for 15-30 minutes as needed or as directed by a doctor.
- Pat dry (do not rub) to keep a thin layer on the skin.

PACKAGE INFORMATION

NDC 49614-191-51
The Medicine Shoppe®
*Compare to active ingredient of Aveeno®
Soothing
Bath Treatment
Regular Formulation
100% Natural Colloidal Oatmeal
Skin Protectant
For fast temporary relief of itching , sore and sensitive skin due to:
Poison Ivy, Poison Sumac, Poison Oak, Insect Bites, Rashes and Eczema
TOTAL NET WEIGHT 12 oz (340 g)
8 INDIVIDUAL USE BATH PACKETS
1.5 oz. (42.5 g) EACH
*This product is not manufactured or distributed by Johnson and Johnson, owner of the registered trademark, Aveeno®.
Distributed by Medicine Shoppe International, Inc.
St. Louis, MO 63132
www.medicineshoppe.com
A Cardinal Health Company
CIN# 3449774